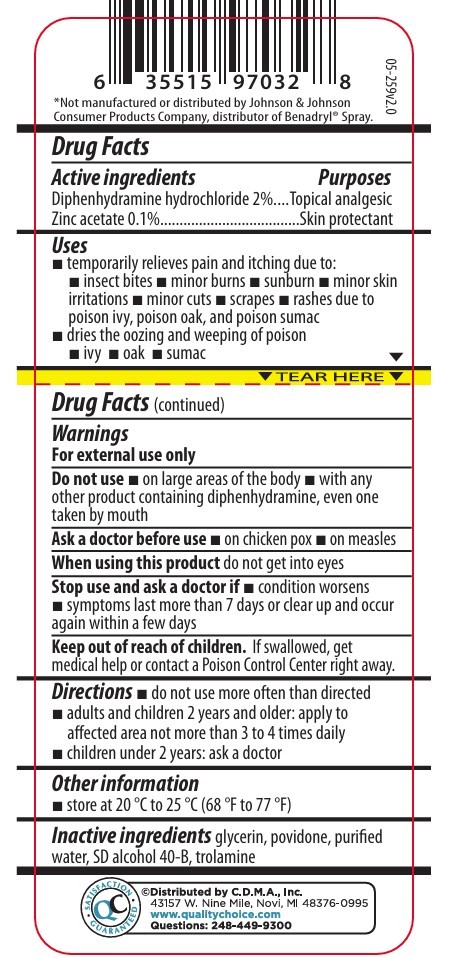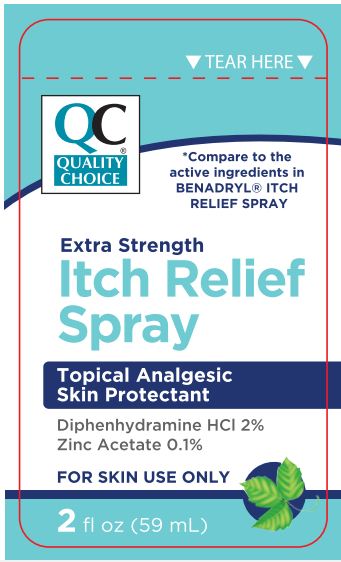 DRUG LABEL: Quality Choice Itch Relief
NDC: 63868-952 | Form: SPRAY
Manufacturer: Chain Drug Marketing Association
Category: otc | Type: HUMAN OTC DRUG LABEL
Date: 20251112

ACTIVE INGREDIENTS: ZINC ACETATE 0.1 g/100 mL; DIPHENHYDRAMINE HYDROCHLORIDE 2 g/100 mL
INACTIVE INGREDIENTS: WATER; GLYCERIN; ALCOHOL; POVIDONE K30; TROLAMINE

Quality Choice Extra Strength Itch Relief Spray

ACTIVE INGREDIENT

Diphenhydramine hydrochloride 2% Topical analgesic

Zinc acetate 0.1% Skin protectant

INDICATIONS AND USAGE

for

temporary relieves pain and itching due to:

insect bites

minor burns

sunburn

minor skin irritations

minor cuts

scrapes

rashes due to poison ivy, poison oak, and poison sumac

dries the oozing and weeping of poison:

ivy

oak

sumac

do not use more often than directed

adults and children 2 years and older: apply to affected area not more than 3 to 4 times daily

children under 2 years: ask a doctor

WARNINGS AND PRECAUTIONS

For external use only

DO NOT USE

on large areas of the body

with any other product containing diphenhydramine, even one taken by mouth

ASK DOCTOR

on chicken pox

on measles

WHEN USING

do not get into eyes

STOP USE

condition worsens

symptoms last more than 7 days or clear up and occur again within a few days

KEEP OUT OF REACH OF CHILDREN

If swallowed, get medical help or contact a Poison Control Center right away.

Warning

for external use only

PURPOSE

Diphenhydramine hydrochloride 2% Topical analgesic

Zinc acetate 0.1% Skin protectant

INACTIVE INGREDIENT

Purified Water, Glycerin, SD Alcohol, Povidone, Povidonee (K-30), Trolamine

PACKAGE LABEL

Quality Choice

Compare to the active ingredients in BENADRYL® ITCH RELIEF SPRAY

Extra Strength Itch Relief Spray

Skin protectant Topical analgesic

Diphenhydramine hydrochloride 2% Zinc acetate 0.1%

For Skin Use Only